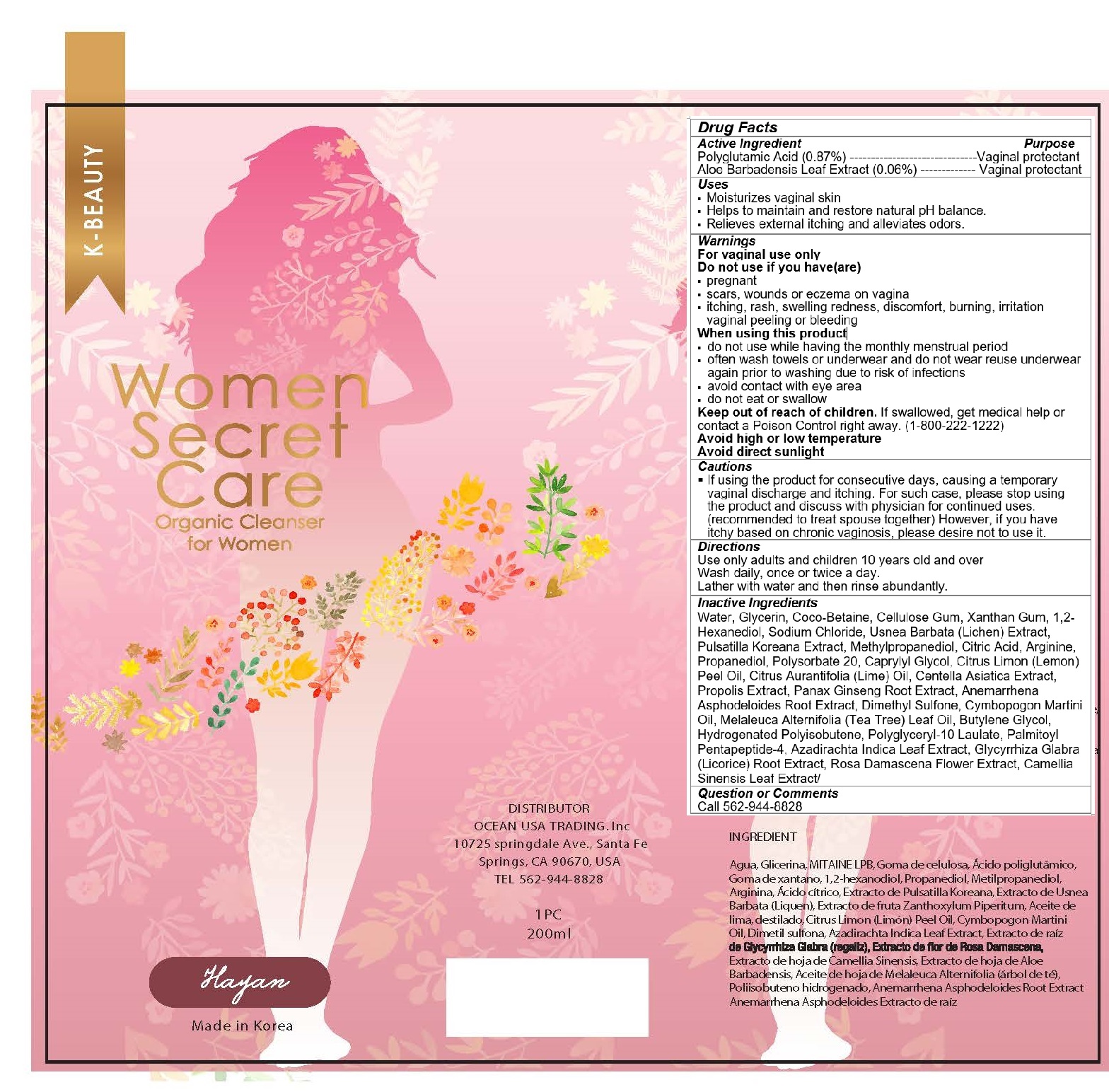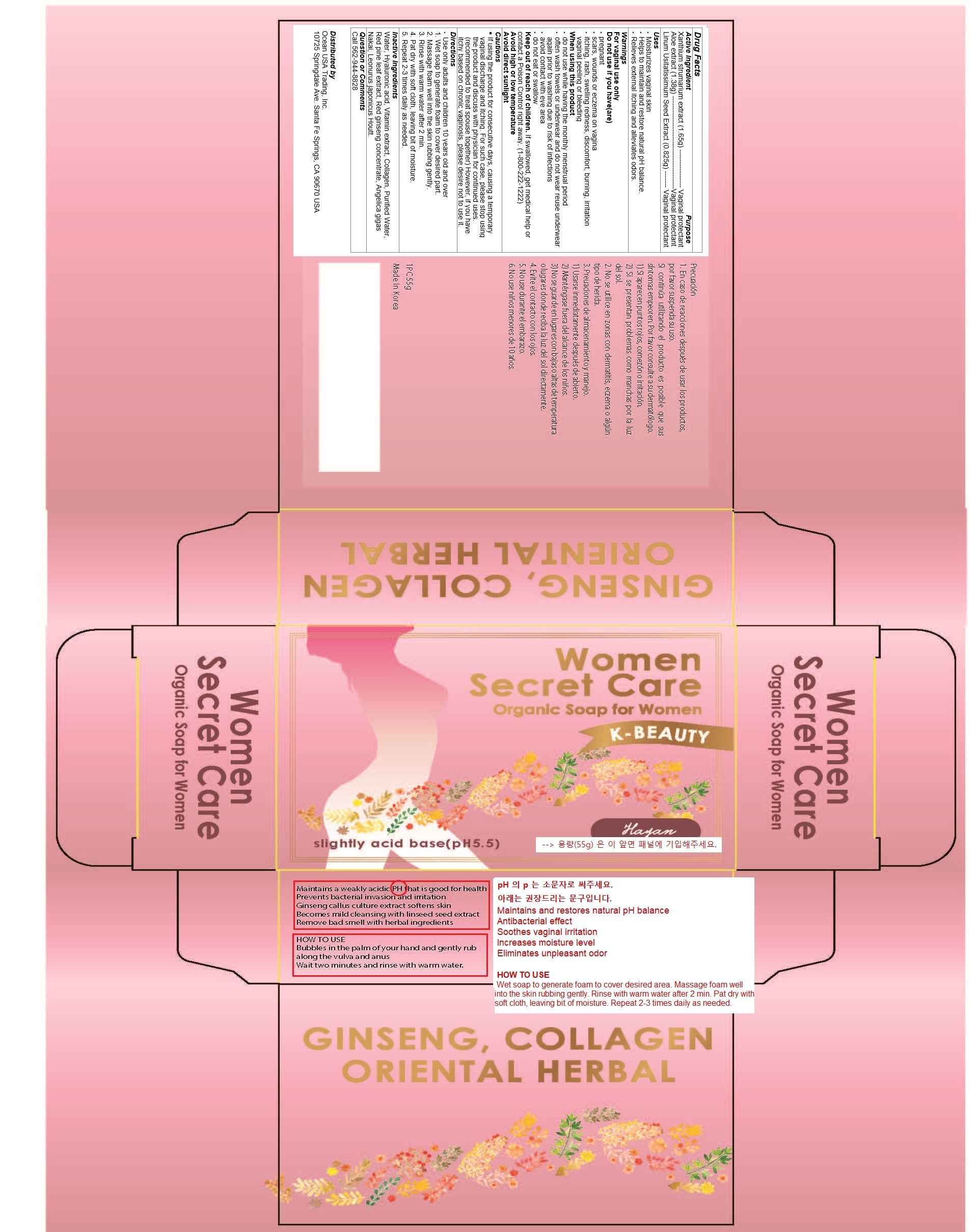 DRUG LABEL: Women Secret Care
NDC: 72530-102 | Form: GEL
Manufacturer: OCEAN USA TRADING INC
Category: otc | Type: HUMAN OTC DRUG LABEL
Date: 20180827

ACTIVE INGREDIENTS: GLUTAMIC ACID 1.74 g/200 g; ALOE 0.12 g/200 g
INACTIVE INGREDIENTS: WATER

WOMEN SECRET CARE GEL

Directions

Use only adults and children 10 years old and over

Wash daily, once or twice a day.

Lather with water and then rinse abundantly.

Inactive Ingredients

Water, Glycerin, Coco-Betaine, Cellulose Gum, Xanthan Gum, 1,2-Hexanediol, Sodium Chloride, Usnea Barbata (Lichen) Extract, Pulsatilla Koreana Extract, Methylpropanediol, Citric Acid, Arginine, Propanediol, Polysorbate 20, Caprylyl Glycol, Citrus Limon (Lemon) Peel Oil, Citrus Aurantifolia (Lime) Oil, Centella Asiatica Extract, Propolis Extract, Panax Ginseng Root Extract, Anemarrhena Asphodeloides Root Extract, Dimethyl Sulfone, Cymbopogon Martini Oil, Melaleuca Alternifolia (Tea Tree) Leaf Oil, Butylene Glycol, Hydrogenated Polyisobutene, Polyglyceryl-10 Laulate, Palmitoyl Pentapeptide-4, Azadirachta Indica Leaf Extract, Glycyrrhiza Glabra (Licorice) Root Extract, Rosa Damascena Flower Extract, Camellia Sinensis Leaf Extract/

Uses

Moisturizes vaginal skin
Helps to maintain and restore natural pH balance.

Relieves external itching and alleviates odors.

Keep out of reach of children

If swallowed, get medical help or contact a Poison Control right away. (1-800-222-1222)

Purpose

Vaginal protectant

Active Ingredient

Polyglutamic Acid (0.87%)

Aloe Barbadensis Leaf Extract (0.06%)

warnings

For vaginal use only

Do not use if you have(are)

pregnant
scars, wounds or eczema on vagina
itching, rash, swelling redness, discomfort, burning, irritation vaginal peeling or bleeding

When using this product

do not use while having the monthly menstrual period
often wash towels or underwear and do not wear reuse underwear again prior to washing due to risk of infections
avoid contact with eye area
do not eat or swallow